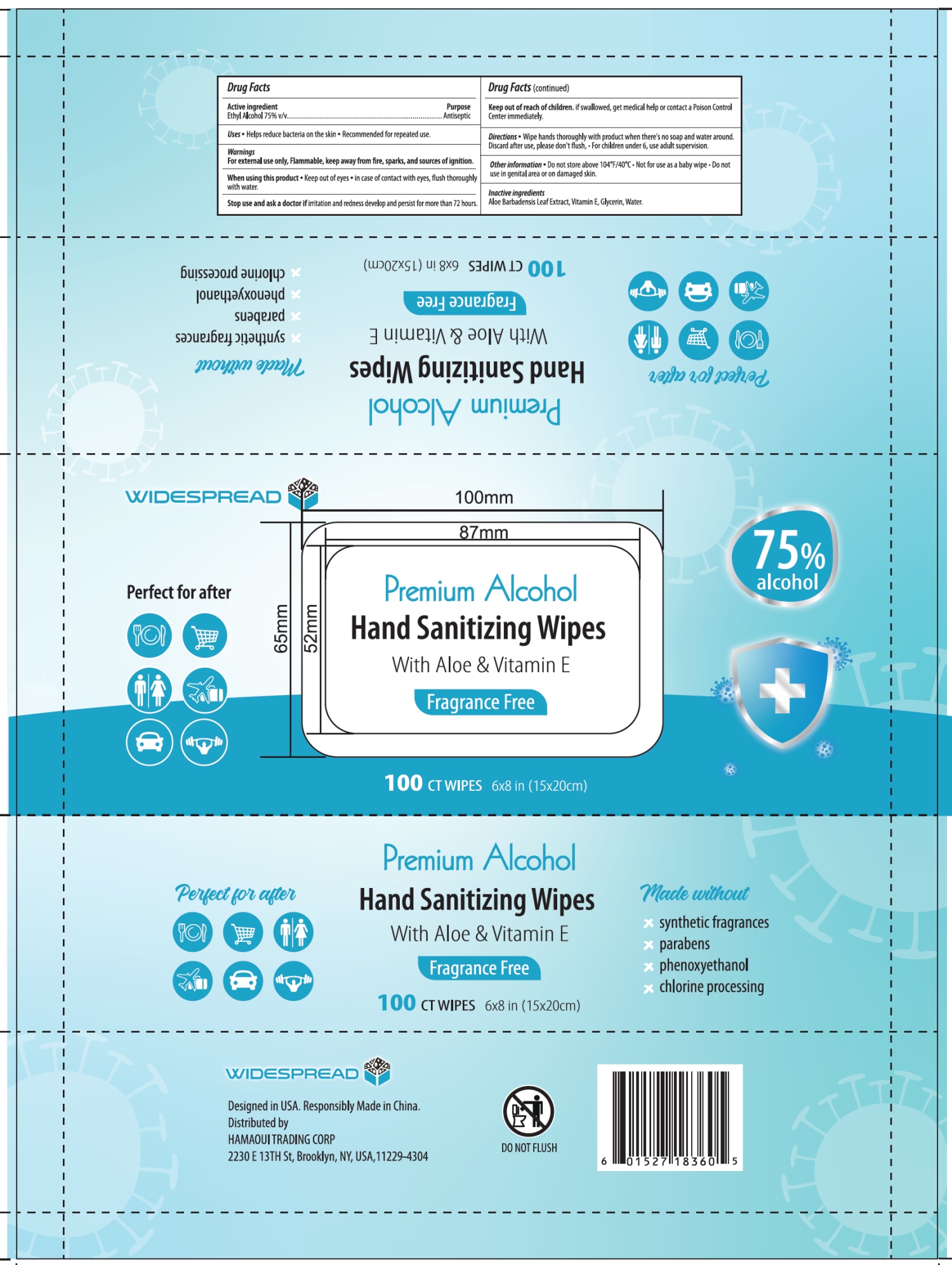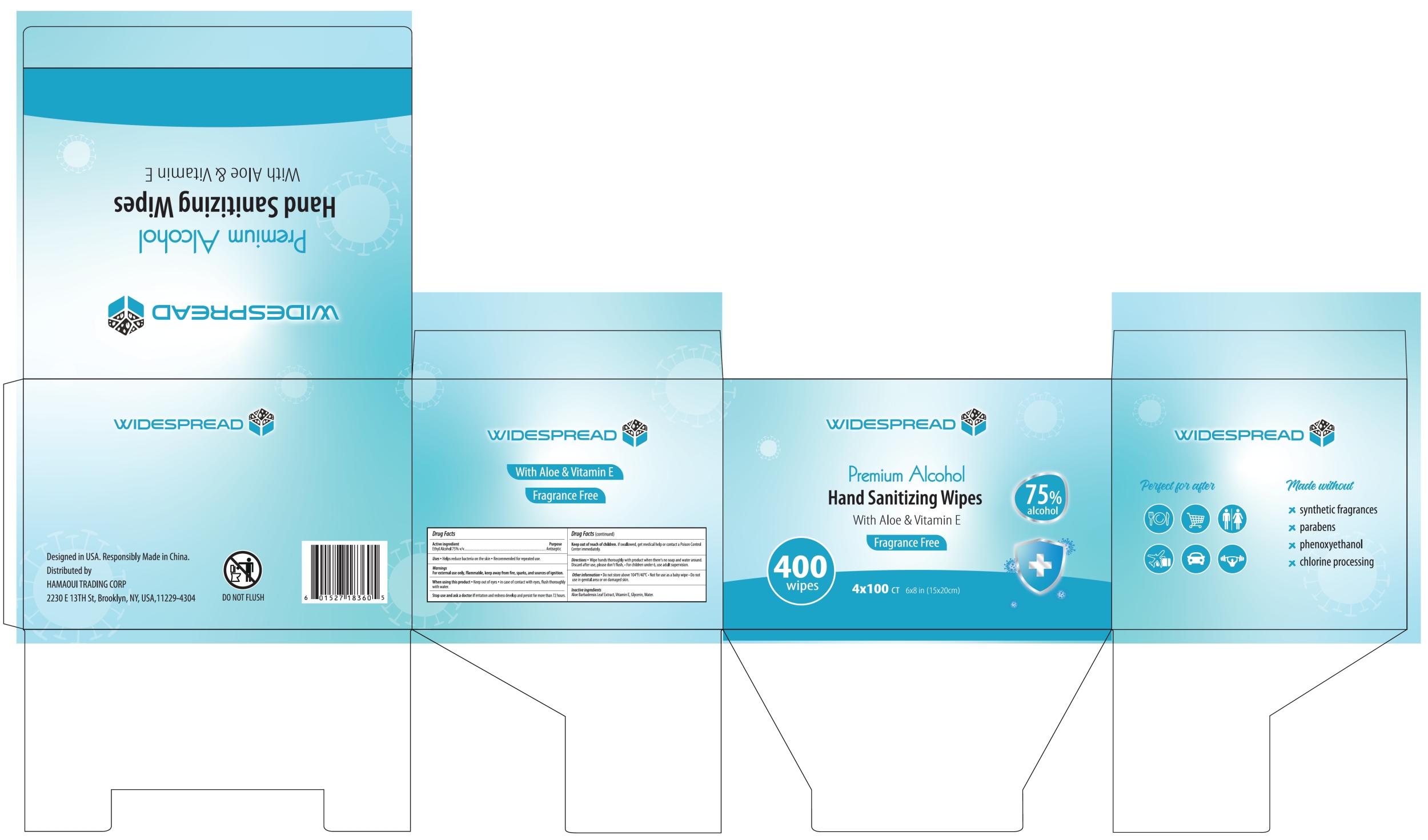 DRUG LABEL: WIDESPREAD Hand Sanitizing Wipes
NDC: 87145-001 | Form: CLOTH
Manufacturer: HAMAOUI TRADING CORP.
Category: otc | Type: HUMAN OTC DRUG LABEL
Date: 20251020

ACTIVE INGREDIENTS: ALCOHOL 75 mL/100 mL
INACTIVE INGREDIENTS: WATER; GLYCERIN; ALOE BARBADENSIS LEAF; .ALPHA.-TOCOPHEROL

87145-001 WIDESPREAD Hand Sanitizing Wipes

Active ingredient

Ethyl Alcohol 75% v/v

Purpose

Antiseptic

INDICATIONS AND USAGE

Uses · Helps reduce bacteria on the skin · Recommended for repeated use.

Warnings

For external use only, Flammable, keep away from fire, sparks, and sources of ignition.

When using this product · Keep out of eyes · in case of contact with eyes, flush thoroughly with water.

Stop use and ask a doctor if irritation and redness develop and persist for more than 72 hours.

Keep out of reach of children. If swallowed, get medical help or contact a Poison Control Center immediately.

DOSAGE AND ADMINISTRATION

Directions · Wipe hands thoroughly with product when there’s no soap and water around. Discard after use, please don’t flush · For children under 6, use adult supervision.

Other information · Do not store above 104℉/40℃ · Not for use as a baby wipe · Do not use in genital area or on damaged skin.

Inactive ingredients

Aloe Barbadensis Leaf Extract, Vitamin E, Glycerin, Water.

PACKAGE LABEL

100 CT WIPES 6×8 in (15×20cm)
NDC: 87145-001-01

400 wipes
4×100 CT 6×8 in (15×20cm)
NDC: 87145-001-02